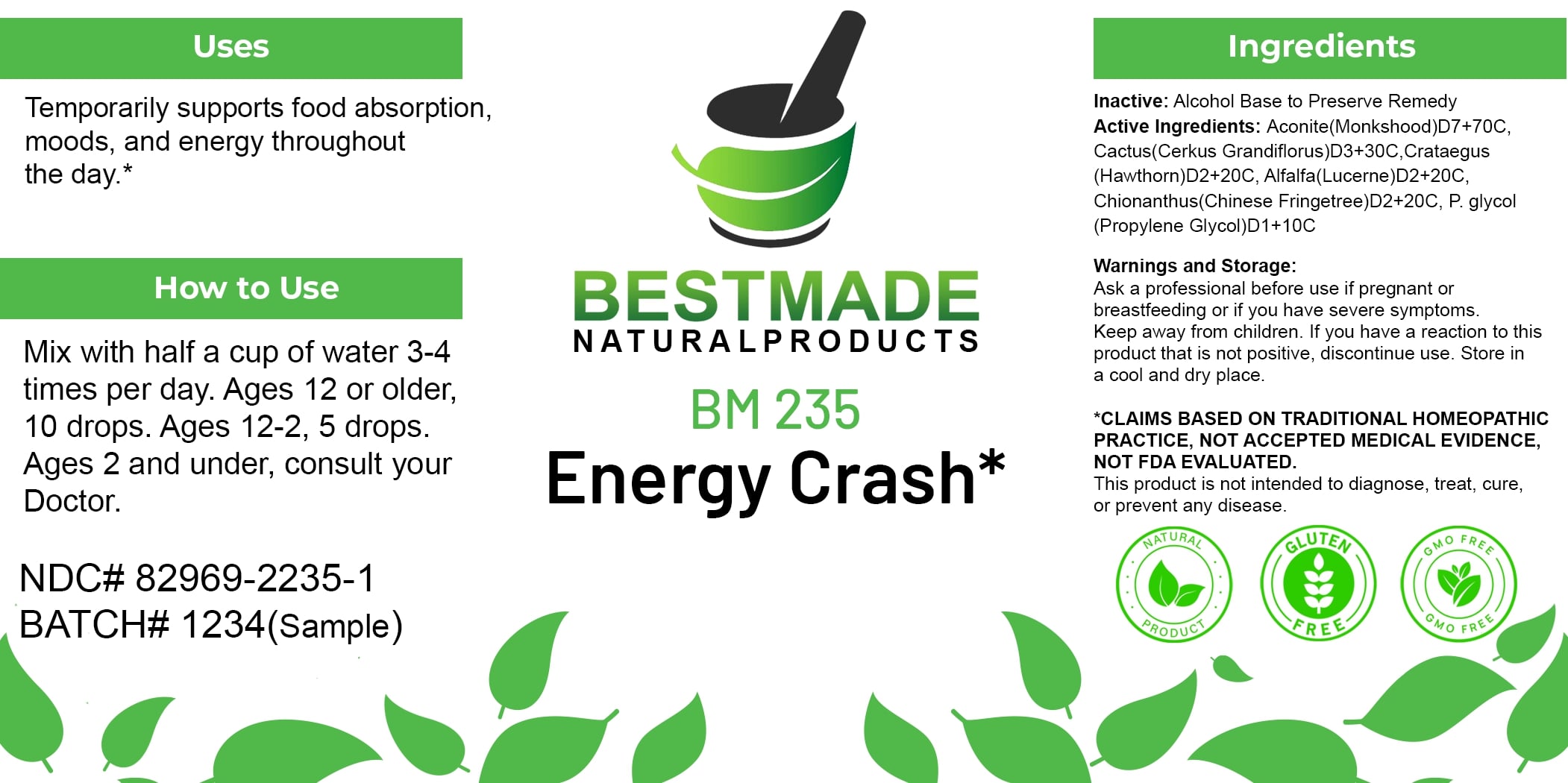 DRUG LABEL: Bestmade Natural Products BM235
NDC: 82969-2235 | Form: LIQUID
Manufacturer: Bestmade Natural Products
Category: homeopathic | Type: HUMAN OTC DRUG LABEL
Date: 20250304

ACTIVE INGREDIENTS: PROPYLENE GLYCOL 30 [hp_C]/30 [hp_C]; ALFALFA 30 [hp_C]/30 [hp_C]; CHIONANTHUS VIRGINICUS ROOT BARK 30 [hp_C]/30 [hp_C]; HAWTHORN LEAF WITH FLOWER 30 [hp_C]/30 [hp_C]; ACONITUM NAPELLUS 30 [hp_C]/30 [hp_C]; SELENICEREUS GRANDIFLORUS STEM 30 [hp_C]/30 [hp_C]
INACTIVE INGREDIENTS: ALCOHOL 30 [hp_C]/30 [hp_C]

BM235

DOSAGE AND ADMINISTRATION

How to Use

Mix with half a cup of water 3-4 times per day. Ages 12 or older, 10 drops. Ages 12-2, 5 drops. Ages 2 and under, consult your Doctor.

Uses

Temporarily supports food absorption, moods, and energy throughout the day.*

*CLAIMS BASED ON TRADITIONAL HOMEOPATHIC PRACTICE, NOT ACCEPTED MEDICAL EVIDENCE. NOT FDA EVALUATED.

This product is not intended to diagnose, treat, cure, or prevent any disease.

INACTIVE INGREDIENT

Ingredients

Inactive: Alcohol Base to Preserve Remedy

ACTIVE INGREDIENT

Active Ingredients: Aconite(Monkshood)D7+70C, Cactus(Cereus Grandiflorus)D3+30C, Crataegus (Hawthorn)D2+20C, Alfalfa(Lucerne)D2+20C, Chionanthus(Chinese Fringetree)D2+20C, P. glycol (Propylene Glycol) D1+10C

KEEP OUT OF REACH OF CHILDREN

Warnings and Storage:

Ask a professional before use if pregnant or breastfeeding or if you have severe symptoms. Keep away from children. If you have a reaction to this product that is not positive, discontinue use. Store in a cool and dry place.

Warnings and Storage:

Ask a professional before use if pregnant or breastfeeding or if you have severe symptoms. Keep away from children. If you have a reaction to this product that is not positive, discontinue use. Store in a cool and dry place.

*CLAIMS BASED ON TRADITIONAL HOMEOPATHIC PRACTICE, NOT ACCEPTED MEDICAL EVIDENCE. NOT FDA EVALUATED.

This product is not intended to diagnose, treat, cure, or prevent any disease.

Uses

Temporarily supports food absorption, moods, and energy throughout the day.*

*CLAIMS BASED ON TRADITIONAL HOMEOPATHIC PRACTICE, NOT ACCEPTED MEDICAL EVIDENCE. NOT FDA EVALUATED.

This product is not intended to diagnose, treat, cure, or prevent any disease.

Entire package label